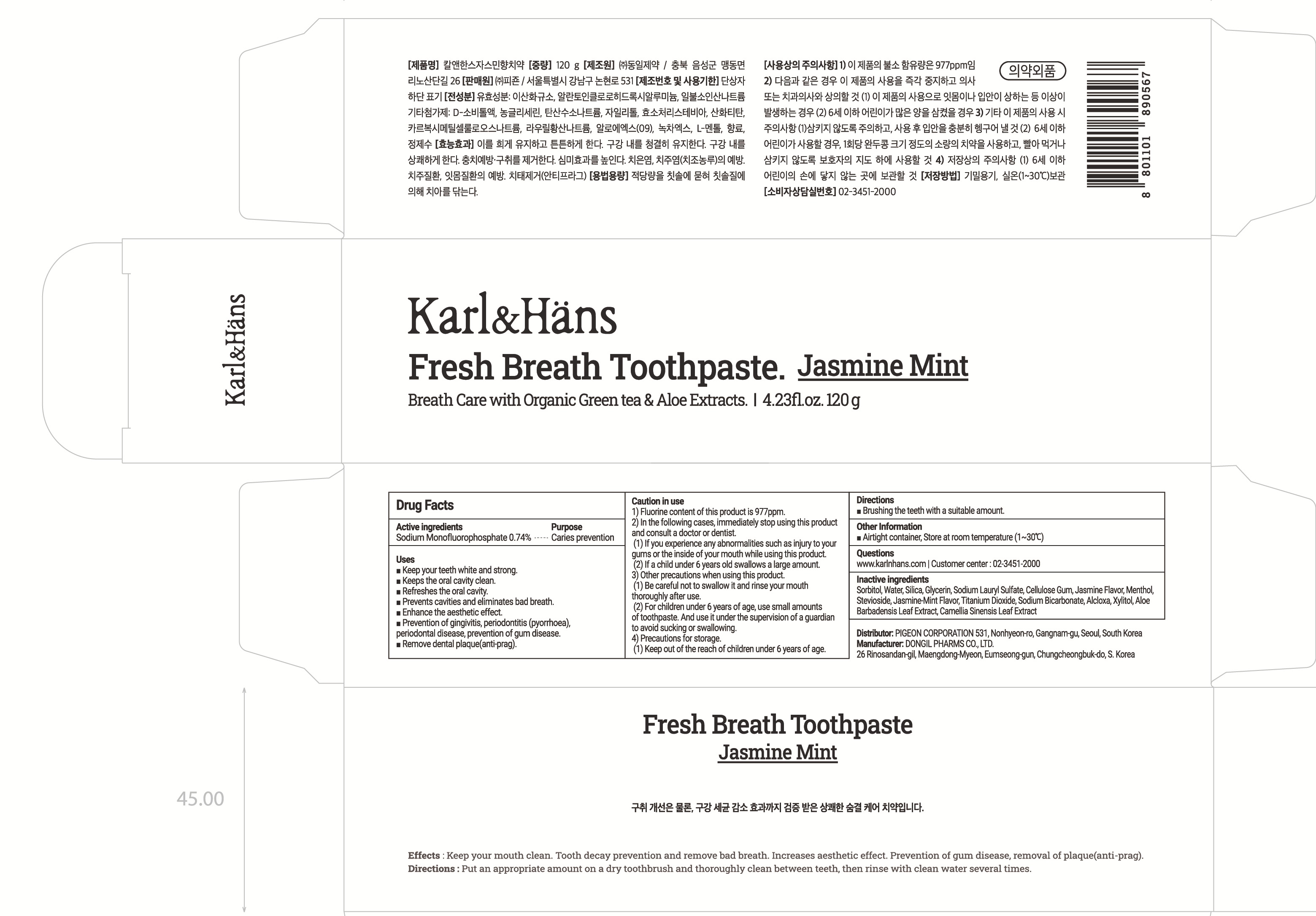 DRUG LABEL: KarlnHans Fresh Breath Jasmine Mint
NDC: 78151-090 | Form: PASTE, DENTIFRICE
Manufacturer: PIGEON CORPORATION
Category: otc | Type: HUMAN OTC DRUG LABEL
Date: 20250623

ACTIVE INGREDIENTS: SODIUM MONOFLUOROPHOSPHATE 0.74 g/100 g
INACTIVE INGREDIENTS: SORBITOL; GLYCERIN; WATER

Drug Facts

ACTIVE INGREDIENT

Sodium Monofluorophosphate 0.74%

INACTIVE INGREDIENT

Sorbitol, Water, Silica, Glycerin, Sodium Lauryl Sulfate, Cellulose Gum, Jasmine Flavor, Menthol, Stevioside, Jasmine-Mint Flavor, Titanium Dioxide, Sodium Bicarbonate, Alcloxa, Xylitol, Aloe Barbadensis Leaf Extract, Camellia Sinensis Leaf Extract

PURPOSE

Caries prevention

WARNINGS

■ Fluorine content of this product is 977ppm.

■ In the following cases, immediately stop using this product and consult a doctor or dentist.

(1) If you experience any abnormalities such as injury to your gums or the inside of your mouth while using this product.

(2) If a child under 6 years old swallows a large amount.

■ Other precautions when using this product.

(1) Be careful not to swallow it and rinse your mouth thoroughly after use.

(2) For children under 6 years of age, use small amounts of toothpaste. And use it under the supervision of a guardian to avoid sucking or swallowing.

■ Precautions for storage.

(1) Keep out of the reach of children under 6 years of age.

KEEP OUT OF REACH OF CHILDREN

■ Keep out of the reach of children under 6 years of age.

Uses

■ Keep your teeth white and strong.

■ Keeps the oral cavity clean.

■ Refreshes the oral cavity.

■ Prevents cavities and eliminates bad breath.

■ Enhance the aesthetic effect.

■ Prevention of gingivitis, periodontitis (pyorrhoea), periodontal disease, prevention of gum disease.

■ Remove dental plaque (anti-prag).

Directions

■ Brushing the teeth with a suitable amount

Other information

■ Airtight container, Store in normal temperature (1~30℃)

Questions

■ www.karlnhans.com | Customer center : 02-3451-2000